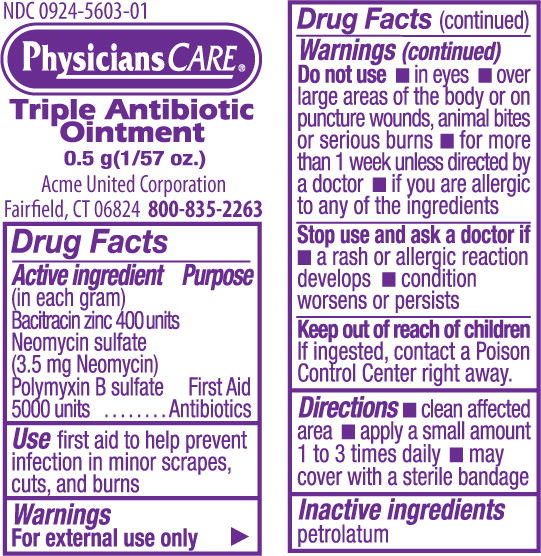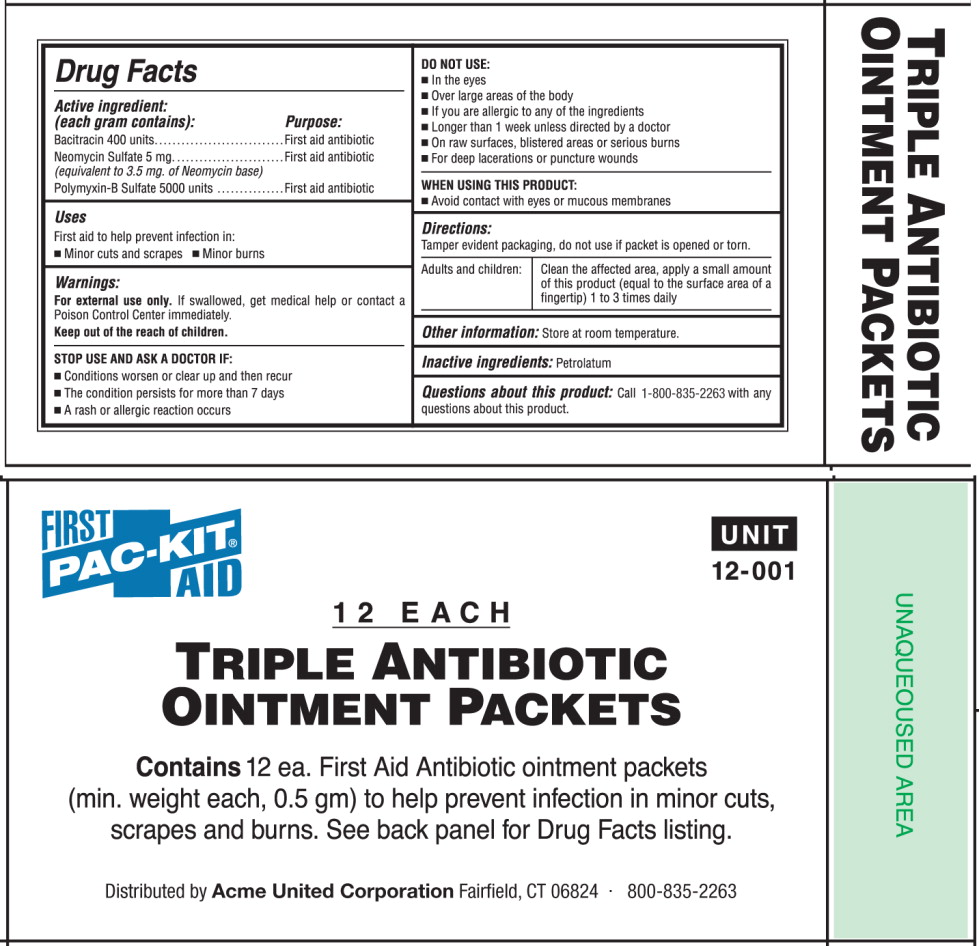 DRUG LABEL: triple antibiotic
NDC: 0924-5603 | Form: OINTMENT
Manufacturer: Acme United Corporation
Category: otc | Type: HUMAN OTC DRUG LABEL
Date: 20120328

ACTIVE INGREDIENTS: bacitracin zinc 400 [iU]/1 g; neomycin sulfate 3.5 mg/1 g; polymyxin b sulfate 5000 [iU]/1 g
INACTIVE INGREDIENTS: petrolatum

Drug Facts

Active Ingredients

(Each gram contains)

Bacitracin 400 units

Neomycin Sulfate 5 mg
(equivalent to 3.5 mg. of Neomycin base)

Polymyxin-B Sulfate 5000 units

Purpose

First Aid Antibiotics

Uses:

First aid to help prevent infection in:

- Minor cuts and scrapes
- Minor burns

Warnings:

For external use only. If swallowed, get medical help or contact a Poison Control Center immediately.

STOP USE AND ASK A DOCTOR IF:

- Conditions worsen or clear up and then recur
- The condition persists for more than 7 days
- A rash or allergic reaction occurs

DO NOT USE:

- In the eyes
- Over large areas of the body
- If you are allergic to any of the ingredients
- Longer than 1 week unless directed by a doctor
- On raw surfaces, blistered areas or serious burns
- For deep lacerations or puncture wounds

WHEN USING THIS PRODUCT:

- Avoid contact with the eyes or mucus membranes

Directions:

Tamper evident packaging, do not use if packet is opened or torn.

Adults and children:

Clean the affected area, apply a small amount of this product (equal to the surface area of a fingertip) 1 to 3 times daily

Other information:

Store at room temperature

Inactive ingredients:

Petrolatum

PRINCIPAL DISPLAY PANEL – packet

NDC 0924-5603-01

PhysiciansCARE

Triple Antibiotic
Ointment

0.5 g (1/57 oz.)

Acme United Corporation

Fairfield, CT 06824 800-835-2263

PRINCIPAL DISPLAY PANEL – 12 count box

PAC-KIT FIRST AID

UNIT
12-001

12 EACH

Triple Antibiotic
Ointment Packets

Contains 12 ea. First Aid Antibiotic ointment packets
(min. weight each, 0.5 gm) to help prevent infection in minor cuts,
scrapes and burns. See back panel for Drug Facts listing.

Distributed by Acme United Corporation Fairfield, CT 06824 · 800-835-2263